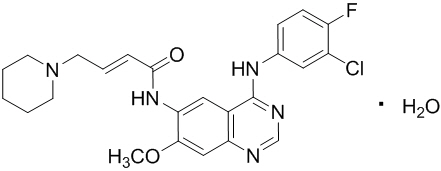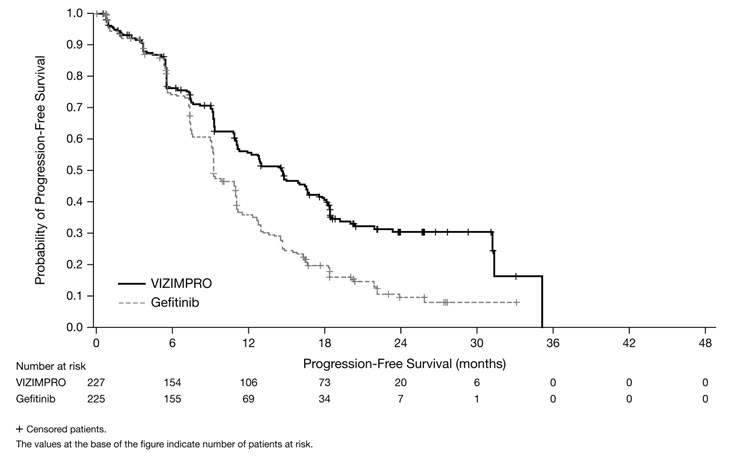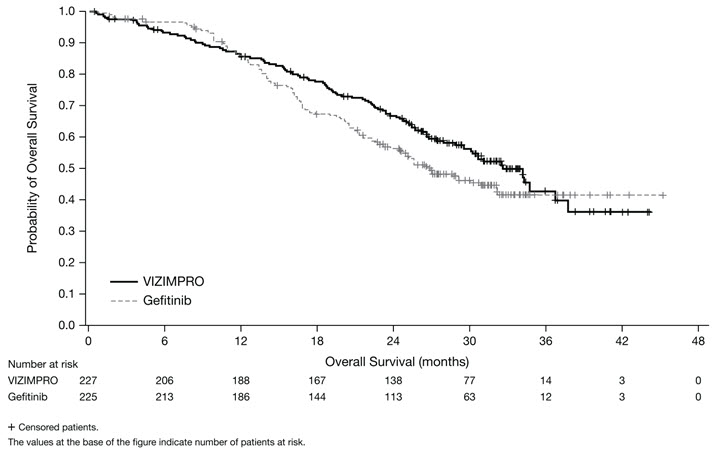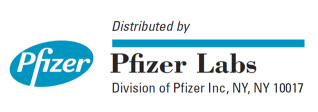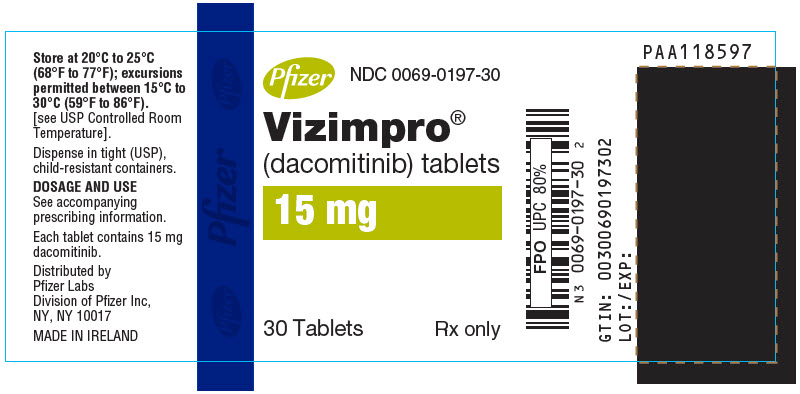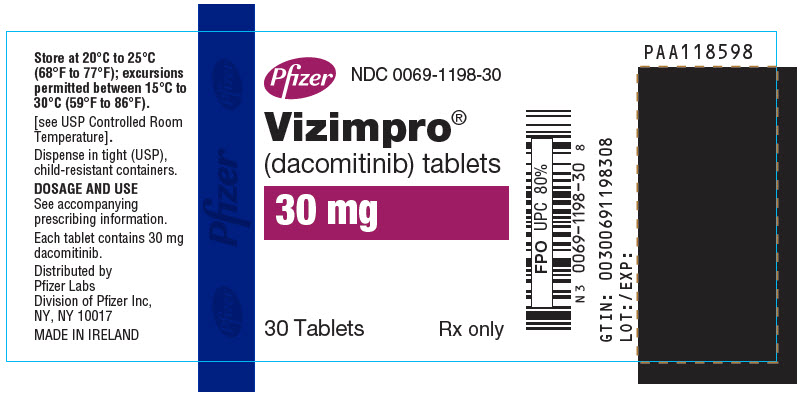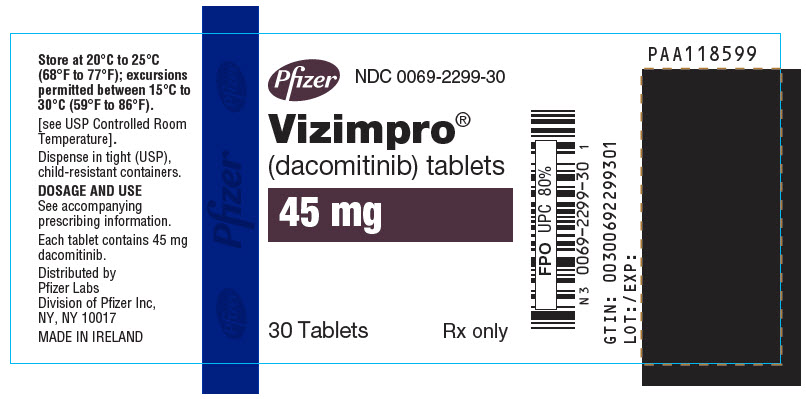 DRUG LABEL: Vizimpro
NDC: 0069-0197 | Form: TABLET, FILM COATED
Manufacturer: Pfizer Laboratories Div Pfizer Inc
Category: prescription | Type: HUMAN PRESCRIPTION DRUG LABEL
Date: 20251218

ACTIVE INGREDIENTS: DACOMITINIB 15 mg/1 1
INACTIVE INGREDIENTS: LACTOSE MONOHYDRATE; MICROCRYSTALLINE CELLULOSE; SODIUM STARCH GLYCOLATE TYPE A POTATO; MAGNESIUM STEARATE; POLYVINYL ALCOHOL, UNSPECIFIED; TALC; TITANIUM DIOXIDE; POLYETHYLENE GLYCOL 3350; FD&C BLUE NO. 2

HIGHLIGHTS OF PRESCRIBING INFORMATION

These highlights do not include all the information needed to use VIZIMPRO safely and effectively. See full prescribing information for VIZIMPRO.
VIZIMPRO® (dacomitinib) tablets, for oral use
Initial U.S. Approval: 2018

1 INDICATIONS AND USAGE

VIZIMPRO is a kinase inhibitor indicated for the first-line treatment of patients with metastatic non-small cell lung cancer (NSCLC) with epidermal growth factor receptor (EGFR) exon 19 deletion or exon 21 L858R substitution mutations as detected by an FDA-approved test. (1)

2 DOSAGE AND ADMINISTRATION

Recommended Dosage: 45 mg orally once daily with or without food. (2.2)

3 DOSAGE FORMS AND STRENGTHS

Tablets: 15 mg, 30 mg, and 45 mg. (3)

4 CONTRAINDICATIONS

None. (4)

5 WARNINGS AND PRECAUTIONS

- Interstitial Lung Disease (ILD): Permanently discontinue VIZIMPRO if ILD is confirmed. (5.1)
- Diarrhea: Withhold and reduce the dose of VIZIMPRO based on the severity. (2.3, 5.2)
- Dermatologic Adverse Reactions: Withhold and reduce the dose of VIZIMPRO based on the severity. (2.3, 5.3)
- Embryo-Fetal Toxicity: VIZIMPRO can cause fetal harm. Advise females of reproductive potential to use effective contraception. (5.4, 8.1, 8.3)

6 ADVERSE REACTIONS

Most common adverse reactions (incidence >20%) are diarrhea, rash, paronychia, stomatitis, decreased appetite, dry skin, decreased weight, alopecia, cough, and pruritus. (6.1)

To report SUSPECTED ADVERSE REACTIONS, contact Pfizer Inc. at 1-800-438-1985 or FDA at 1-800-FDA-1088 or www.fda.gov/medwatch.

7 DRUG INTERACTIONS

- Proton Pump Inhibitors (PPIs): Avoid use with VIZIMPRO; use locally-acting antacids or H2-receptor antagonist; administer VIZIMPRO at least 6 hours before or 10 hours after H2-receptor antagonist. (2.4, 7.1)
- CYP2D6 Substrates: Avoid concomitant use with VIZIMPRO where minimal increases in concentration of the CYP2D6 substrate may lead to serious or life-threatening toxicities. (7.2)

8 USE IN SPECIFIC POPULATIONS

- Lactation: Advise not to breastfeed. (8.2)

FULL PRESCRIBING INFORMATION

1 INDICATIONS AND USAGE

VIZIMPRO is indicated for the first-line treatment of patients with metastatic non-small cell lung cancer (NSCLC) with epidermal growth factor receptor (EGFR) exon 19 deletion or exon 21 L858R substitution mutations as detected by an FDA-approved test [see Dosage and Administration (2.1)].

2 DOSAGE AND ADMINISTRATION

2.1 Patient Selection

Select patients for the first-line treatment of metastatic NSCLC with VIZIMPRO based on the presence of an EGFR exon 19 deletion or exon 21 L858R substitution mutation in tumor specimens. Information on FDA-approved tests for the detection of EGFR mutations in NSCLC is available at: http://www.fda.gov/CompanionDiagnostics.

2.2 Recommended Dosage

The recommended dosage of VIZIMPRO is 45 mg taken orally once daily, until disease progression or unacceptable toxicity occurs. VIZIMPRO can be taken with or without food [see Dosage and Administration (2.4) and Clinical Pharmacology (12.3)].

Take VIZIMPRO the same time each day. If the patient vomits or misses a dose, do not take an additional dose or make up a missed dose but continue with the next scheduled dose.

2.3 Dosage Modifications for Adverse Reactions

Reduce the dose of VIZIMPRO for adverse reactions as described in Table 1. Dosage modifications for specific adverse reactions are provided in Table 2.

Table 1. VIZIMPRO Recommended Dose Reductions for Adverse Reactions
Dose Level | Dose (Once Daily)
First dose reduction | 30 mg
Second dose reduction | 15 mg

Table 2. VIZIMPRO Dosage Modifications for Adverse Reactions
Adverse Reaction | Severity [National Cancer Institute Common Terminology Criteria for Adverse Events Version 4.03.] | Dosage Modification
Interstitial lung disease (ILD) [see Warnings and Precautions (5.1)] | Any Grade | - Permanently discontinue VIZIMPRO.
Diarrhea [see Warnings and Precautions (5.2)] | Grade 2 | - Withhold VIZIMPRO until recovery to less than or equal to Grade 1; then resume VIZIMPRO at the same dose level. - For recurrent Grade 2 diarrhea, withhold until recovery to less than or equal to Grade 1; then resume VIZIMPRO at a reduced dose.
Diarrhea [see Warnings and Precautions (5.2)] | Grade 3 or 4 | - Withhold VIZIMPRO until recovery to less than or equal to Grade 1; then resume VIZIMPRO at a reduced dose.
Dermatologic Adverse Reactions [see Warnings and Precautions (5.3)] | Grade 2 | - Withhold VIZIMPRO for persistent dermatologic adverse reactions; upon recovery to less than or equal to Grade 1, resume VIZIMPRO at the same dose level. - For recurrent persistent Grade 2 dermatologic adverse reactions, withhold until recovery to less than or equal to Grade 1; then resume VIZIMPRO at a reduced dose.
Dermatologic Adverse Reactions [see Warnings and Precautions (5.3)] | Grade 3 or 4 | - Withhold VIZIMPRO until recovery to less than or equal to Grade 1; then resume VIZIMPRO at a reduced dose.
Other | Grade 3 or 4 | - Withhold VIZIMPRO until recovery to less than or equal to Grade 2; then resume VIZIMPRO at a reduced dose.

2.4 Dosage Modifications for Acid-Reducing Agents

Avoid the concomitant use of proton pump inhibitors (PPIs) while taking VIZIMPRO. As an alternative to PPIs, use locally-acting antacids or if using an histamine 2 (H2)-receptor antagonist, administer VIZIMPRO at least 6 hours before or 10 hours after taking an H2-receptor antagonist [see Drug Interactions (7.1) and Clinical Pharmacology (12.3)].

3 DOSAGE FORMS AND STRENGTHS

Tablets:

- 45 mg: blue film-coated, immediate release, round biconvex tablet, debossed with "Pfizer" on one side and "DCB45" on the other side.
- 30 mg: blue film-coated, immediate release, round biconvex tablet, debossed with "Pfizer" on one side and "DCB30" on the other side.
- 15 mg: blue film-coated, immediate release, round biconvex tablet, debossed with "Pfizer" on one side and "DCB15" on the other side.

4 CONTRAINDICATIONS

None.

5 WARNINGS AND PRECAUTIONS

5.1 Interstitial Lung Disease (ILD)

Severe and fatal ILD/pneumonitis occurred in patients treated with VIZIMPRO and occurred in 0.5% of the 394 VIZIMPRO-treated patients; 0.3% of cases were fatal.

Monitor patients for pulmonary symptoms indicative of ILD/pneumonitis. Withhold VIZIMPRO and promptly investigate for ILD in patients who present with worsening of respiratory symptoms which may be indicative of ILD (e.g., dyspnea, cough, and fever). Permanently discontinue VIZIMPRO if ILD is confirmed [see Adverse Reactions (6.1)].

5.2 Diarrhea

Severe and fatal diarrhea occurred in patients treated with VIZIMPRO. Diarrhea occurred in 86% of the 394 VIZIMPRO-treated patients; Grade 3 or 4 diarrhea was reported in 11% of patients and 0.3% of cases were fatal.

Withhold VIZIMPRO for Grade 2 or greater diarrhea until recovery to less than or equal to Grade 1 severity, then resume VIZIMPRO at the same or a reduced dose depending on the severity of diarrhea [see Dosage and Administration (2.3) and Adverse Reactions (6.1)]. Promptly initiate anti-diarrheal treatment (loperamide or diphenoxylate hydrochloride with atropine sulfate) for diarrhea.

5.3 Dermatologic Adverse Reactions

Rash and exfoliative skin reactions occurred in patients treated with VIZIMPRO. Rash occurred in 78% of the 394 VIZIMPRO-treated patients; Grade 3 or 4 rash was reported in 21% of patients. Exfoliative skin reactions of any severity were reported in 7% of patients. Grade 3 or 4 exfoliative skin reactions were reported in 1.8% of patients.

Withhold VIZIMPRO for persistent Grade 2 or any Grade 3 or 4 dermatologic adverse reaction until recovery to less than or equal to Grade 1 severity, then resume VIZIMPRO at the same or a reduced dose depending on the severity of the dermatologic adverse reaction [see Dosage and Administration (2.3) and Adverse Reactions (6.1)]. The incidence and severity of rash and exfoliative skin reactions may increase with sun exposure. At the time of initiation of VIZIMPRO, initiate use of moisturizers and appropriate measures to limit sun exposure. Upon development of Grade 1 rash, initiate treatment with topical antibiotics and topical steroids. Initiate oral antibiotics for Grade 2 or more severe dermatologic adverse reactions.

5.4 Embryo-Fetal Toxicity

Based on findings from animal studies and its mechanism of action, VIZIMPRO can cause fetal harm when administered to a pregnant woman. In animal reproduction studies, oral administration of dacomitinib to pregnant rats during the period of organogenesis resulted in an increased incidence of post-implantation loss and reduced fetal body weight at doses resulting in exposures near the exposure at the 45 mg human dose. The absence of EGFR signaling has been shown to result in embryolethality as well as post-natal death in animals. Advise pregnant women of the potential risk to the fetus. Advise females of reproductive potential to use effective contraception during treatment with VIZIMPRO and for at least 17 days after the final dose [see Use in Specific Populations (8.1 and 8.3)].

6 ADVERSE REACTIONS

The following adverse drug reactions are described elsewhere in the labeling:

- Interstitial Lung Disease [see Warnings and Precautions (5.1)]
- Diarrhea [see Warnings and Precautions (5.2)]
- Dermatologic Adverse Reactions [see Warnings and Precautions (5.3)]

6.1 Clinical Trials Experience

Because clinical trials are conducted under widely varying conditions, adverse reaction rates observed in the clinical trials of a drug cannot be directly compared to rates in the clinical trials of another drug and may not reflect the rates observed in practice.

The data in the Warnings and Precautions section reflect exposure to VIZIMPRO in 394 patients with first-line or previously treated NSCLC with EGFR exon 19 deletion or exon 21 L858R substitution mutations who received VIZIMPRO at the recommended dose of 45 mg once daily in 4 randomized, active-controlled trials [ARCHER 1050 (N=227), Study A7471009 (N=38), Study A7471011 (N=83), and Study A7471028 (N=16)] and one single-arm trial [Study A7471017 (N=30)]. The median duration of exposure to VIZIMPRO was 10.8 months (range 0.07–68) [see Warnings and Precautions (5)].

The data described below reflect exposure to VIZIMPRO in 227 patients with EGFR mutation-positive, metastatic NSCLC enrolled in a randomized, active-controlled trial (ARCHER 1050); 224 patients received gefitinib 250 mg orally once daily in the active control arm [see Clinical Studies (14)]. Patients were excluded if they had a history of ILD, interstitial pneumonitis, or brain metastases. The median duration of exposure to VIZIMPRO was 15 months (range 0.07–37).

The most common (>20%) adverse reactions in patients treated with VIZIMPRO were diarrhea (87%), rash (69%), paronychia (64%), stomatitis (45%), decreased appetite (31%), dry skin (30%), decreased weight (26%), alopecia (23%), cough (21%), and pruritus (21%).

Serious adverse reactions occurred in 27% of patients treated with VIZIMPRO. The most common (≥1%) serious adverse reactions were diarrhea (2.2%) and interstitial lung disease (1.3%). Dose interruptions occurred in 57% of patients treated with VIZIMPRO. The most frequent (>5%) adverse reactions leading to dose interruptions were rash (23%), paronychia (13%), and diarrhea (10%). Dose reductions occurred in 66% of patients treated with VIZIMPRO. The most frequent (>5%) adverse reactions leading to dose reductions were rash (29%), paronychia (17%), and diarrhea (8%).

Adverse reactions leading to permanent discontinuation of VIZIMPRO occurred in 18% of patients. The most common (>0.5%) adverse reactions leading to permanent discontinuation of VIZIMPRO were: rash (2.6%), interstitial lung disease (1.8%), stomatitis (0.9%), and diarrhea (0.9%).

Tables 3 and 4 summarize the most common adverse reactions and laboratory abnormalities, respectively, in ARCHER 1050. ARCHER 1050 was not designed to demonstrate a statistically significant difference in adverse reaction rates for VIZIMPRO or for gefitinib for any adverse reaction or laboratory value listed in Table 3 or 4.

Table 3. Adverse Reactions Occurring in ≥10% of Patients Receiving VIZIMPRO in ARCHER 1050 [National Cancer Institute Common Terminology Criteria for Adverse Events (NCI CTCAE) v4.03.]
Adverse Reaction | VIZIMPRO (N=227) |  | Gefitinib (N=224)
 | All Grades [Grades 1 through 5 are included in All Grades.] % | Grades 3 and 4 % | All Grades % | Grades 3 and 4 %
Gastrointestinal
Diarrhea [One Grade 5 (fatal) event in the VIZIMPRO arm.] | 87 | 8 | 56 | 0.9
Stomatitis [Stomatitis includes mucosal inflammation and stomatitis.] | 45 | 4.4 | 19 | 0.4
Nausea | 19 | 1.3 | 22 | 0.4
Constipation | 13 | 0 | 14 | 0
Mouth ulceration | 12 | 0 | 6 | 0
Skin and Subcutaneous Tissue
Rash [Rash includes dermatitis acneiform, rash, and rash maculo-papular.] | 69 | 23 | 47 | 0.4
Paronychia [Paronychia includes nail infection, nail toxicity, onychoclasis, onycholysis, onychomadesis, paronychia.] | 64 | 8 | 21 | 1.3
Dry skin [Dry skin includes dry skin, xerosis.] | 30 | 1.8 | 19 | 0.4
Alopecia | 23 | 0.4 | 13 | 0
Pruritus [Pruritus includes pruritus, pruritus generalized, rash pruritic.] | 21 | 0.9 | 15 | 1.3
Palmar-plantar erythrodysesthesia syndrome | 15 | 0.9 | 3.1 | 0
Dermatitis | 11 | 1.8 | 4 | 0.4
Metabolism and Nutrition
Decreased appetite | 31 | 3.1 | 25 | 0.4
Decreased weight | 26 | 2.2 | 17 | 0.4
Respiratory
Cough | 21 | 0 | 19 | 0.4
Nasal mucosal disorder [Nasal mucosal disorder includes epistaxis, nasal inflammation, nasal mucosal disorder, nasal mucosal ulcer, rhinitis.] | 19 | 0 | 4.9 | 0
Dyspnea | 13 | 2.2 | 13 | 1.8
Upper respiratory tract infection | 12 | 1.3 | 13 | 0
Chest pain | 10 | 0 | 14 | 0
Eye
Conjunctivitis | 19 | 0 | 4 | 0
Musculoskeletal
Pain in extremity | 14 | 0 | 12 | 0
Musculoskeletal pain | 12 | 0.9 | 13 | 0
General
Asthenia | 13 | 2.2 | 13 | 1.3
Psychiatric
Insomnia | 11 | 0.4 | 15 | 0

Additional adverse reactions (All Grades) that were reported in <10% of patients who received VIZIMPRO in ARCHER 1050 include:

General: fatigue 9%

Skin and subcutaneous tissue: skin fissures 9%, hypertrichosis 1.3%, skin exfoliation/exfoliative skin reactions 3.5%

Gastrointestinal: vomiting 9%

Nervous system: dysgeusia 7%

Respiratory: interstitial lung disease 2.6%

Ocular: keratitis 1.8%

Metabolism and nutrition: dehydration 1.3%

Table 4. Laboratory Abnormalities Worsening from Baseline in >20% of Patients in ARCHER 1050 [NCI CTCAE v4.03, except for increased creatinine which only includes patients with creatinine increase based on upper limit of normal definition.]
Laboratory Test Abnormality [Based on the number of patients with available baseline and at least one on-treatment laboratory test.] | VIZIMPRO |  | Gefitinib
Laboratory Test Abnormality [Based on the number of patients with available baseline and at least one on-treatment laboratory test.] | Change from Baseline All Grades (%) | Change from Baseline to Grade 3 or Grade 4 (%) | Change from Baseline All Grades (%) | Change from Baseline to Grade 3 or Grade 4 (%)
Hematology
Anemia | 44 | 0.9 | 26 | 2.7
Lymphopenia | 42 | 6 | 35 | 2.7
Chemistry
Hypoalbuminemia | 44 | 0 | 34 | 0
Increased ALT | 40 | 1.4 | 63 | 13
Hyperglycemia | 36 | 1.0 | 38 | 2.5
Increased AST | 35 | 0.5 | 57 | 8
Hypocalcemia | 33 | 1.4 | 28 | 2.0
Hypokalemia | 29 | 7 | 18 | 2.0
Hyponatremia | 26 | 2.9 | 20 | 1.5
Increased creatinine | 24 | 0 | 16 | 0.5
Increased alkaline phosphatase | 22 | 0.5 | 21 | 2.0
Hypomagnesemia | 22 | 0.5 | 9 | 0
Hyperbilirubinemia | 16 | 0.5 | 22 | 0.5
ALT=alanine aminotransferase; AST=aspartate aminotransferase.

7 DRUG INTERACTIONS

7.1 Effect of Other Drugs on VIZIMPRO

Concomitant use with a PPI decreases dacomitinib concentrations, which may reduce VIZIMPRO efficacy. Avoid the concomitant use of PPIs with VIZIMPRO. As an alternative to PPIs, use locally-acting antacids or an H2-receptor antagonist. Administer VIZIMPRO at least 6 hours before or 10 hours after taking an H2-receptor antagonist [see Dosage and Administration (2.4) and Clinical Pharmacology (12.3)].

7.2 Effect of VIZIMPRO on CYP2D6 Substrates

Concomitant use of VIZIMPRO increases the concentration of drugs that are CYP2D6 substrates [see Clinical Pharmacology (12.3)] which may increase the risk of toxicities of these drugs. Avoid concomitant use of VIZIMPRO with CYP2D6 substrates where minimal increases in concentration of the CYP2D6 substrate may lead to serious or life-threatening toxicities.

8 USE IN SPECIFIC POPULATIONS

8.1 Pregnancy

Risk Summary

Based on findings from animal studies and its mechanism of action, VIZIMPRO can cause fetal harm when administered to a pregnant woman [see Clinical Pharmacology (12.1)]. There are no available data on VIZIMPRO use in pregnant women. In animal reproduction studies, oral administration of dacomitinib to pregnant rats during the period of organogenesis resulted in an increased incidence of post-implantation loss and reduced fetal body weight at doses resulting in exposures near the exposure at the 45 mg human dose (see Data). The absence of EGFR signaling has been shown to result in embryolethality as well as post-natal death in animals (see Data). Advise pregnant women of the potential risk to a fetus [see Use in Special Populations (8.3)].

In the U.S. general population, the estimated background risk of major birth defects and miscarriage in clinically recognized pregnancies is 2% to 4% and 15% to 20%, respectively.

Data

Animal Data

Daily oral administration of dacomitinib to pregnant rats during the period of organogenesis resulted in an increased incidence of post-implantation loss, maternal toxicity, and reduced fetal body weight at 5 mg/kg/day (approximately 1.2 times the exposure based on area under the curve [AUC] at the 45 mg human dose).

Disruption or depletion of EGFR in mouse models has shown EGFR is critically important in reproductive and developmental processes including blastocyst implantation, placental development, and embryo-fetal/post-natal survival and development. Reduction or elimination of embryo-fetal or maternal EGFR signaling in mice can prevent implantation, and can cause embryo-fetal loss during various stages of gestation (through effects on placental development), developmental anomalies, early death in surviving fetuses, and adverse developmental outcomes in multiple organs in embryos/neonates.

8.2 Lactation

Risk Summary

There is no information regarding the presence of dacomitinib or its metabolites in human milk or their effects on the breastfed infant or on milk production. Because of the potential for serious adverse reactions in breastfed infants from VIZIMPRO, advise women not to breastfeed during treatment with VIZIMPRO and for at least 17 days after the last dose.

8.3 Females and Males of Reproductive Potential

Pregnancy Testing

Verify the pregnancy status of females of reproductive potential prior to initiating VIZIMPRO [see Use in Specific Populations (8.1)].

Contraception

VIZIMPRO can cause fetal harm when administered to a pregnant woman [see Use in Specific Populations (8.1)].

Females

Advise females of reproductive potential to use effective contraception during treatment with VIZIMPRO and for at least 17 days after the final dose.

8.4 Pediatric Use

The safety and effectiveness of VIZIMPRO in pediatrics have not been established.

8.5 Geriatric Use

Of the total number of patients (N=394) in five clinical studies with EGFR mutation-positive NSCLC who received VIZIMPRO at a dose of 45 mg orally once daily [ARCHER 1050 (N=227), Study A7471009 (N=38), Study A7471011 (N=83), Study A7471028 (N=16), and Study A7471017 (N=30)] 40% were 65 years of age and older.

Exploratory analyses across this population suggest a higher incidence of Grade 3 and 4 adverse reactions (67% versus 56%, respectively), more frequent dose interruptions (53% versus 45%, respectively), and more frequent discontinuations (24% versus 10%, respectively) for adverse reactions in patients 65 years or older as compared to those younger than 65 years.

8.6 Renal Impairment

No dosage modification is recommended for patients with mild or moderate renal impairment (creatinine clearance [CLcr] 30 to 89 mL/min estimated by Cockcroft-Gault). The recommended dose of VIZIMPRO has not been established for patients with severe renal impairment (CLcr <30 mL/min) [see Clinical Pharmacology (12.3)].

8.7 Hepatic Impairment

No dosage modification is recommended in patients with mild, moderate or severe hepatic impairment (Child-Pugh A, B or C) [see Clinical Pharmacology (12.3)].

11 DESCRIPTION

Dacomitinib is an oral kinase inhibitor with a molecular formula of C24H25ClFN5O2 ∙ H2O and a molecular weight of 487.95 Daltons. The chemical name is: (2E)-N-{4-[(3-Chloro-4-fluorophenyl)amino]-7-methoxyquinazolin-6-yl}-4-(piperidin-1-yl)but-2-enamide monohydrate and its structural formula is:

Dacomitinib is a white to pale yellow powder.

VIZIMPRO tablets contain 45, 30, or 15 mg of dacomitinib with the following inactive ingredients in the tablet core; lactose monohydrate, microcrystalline cellulose, sodium starch glycolate, and magnesium stearate. The film coating consists of Opadry II® Blue 85F30716 containing: Polyvinyl alcohol – partially hydrolyzed, Talc, Titanium dioxide, Macrogol/PEG 3350, and FD&C Blue #2/Indigo Carmine Aluminum Lake.

12 CLINICAL PHARMACOLOGY

12.1 Mechanism of Action

Dacomitinib is an irreversible inhibitor of the kinase activity of the human EGFR family (EGFR/HER1, HER2, and HER4) and certain EGFR activating mutations (exon 19 deletion or the exon 21 L858R substitution mutation). In vitro dacomitinib also inhibited the activity of DDR1, EPHA6, LCK, DDR2, and MNK1 at clinically relevant concentrations.

Dacomitinib demonstrated dose-dependent inhibition of EGFR and HER2 autophosphorylation and tumor growth in mice bearing subcutaneously implanted human tumor xenografts driven by HER family targets including mutated EGFR. Dacomitinib also exhibited antitumor activity in orally-dosed mice bearing intracranial human tumor xenografts driven by EGFR amplifications.

12.2 Pharmacodynamics

Cardiac Electrophysiology

The effect of dacomitinib on the QT interval corrected for heart rate (QTc) was evaluated using time-matched electrocardiograms (ECGs) evaluating the change from baseline and corresponding pharmacokinetic data in 32 patients with advanced NSCLC. Dacomitinib had no large effect on QTc (i.e., >20 ms) at maximum dacomitinib concentrations achieved with VIZIMPRO 45 mg orally once daily.

Exposure-Response Relationships

Higher exposures, across the range of exposures with the recommended dose of 45 mg daily, correlated with an increased probability of Grade ≥3 adverse events, specifically dermatologic toxicities and diarrhea.

12.3 Pharmacokinetics

The maximum dacomitinib plasma concentration (Cmax) and AUC at steady state increased proportionally over the dose range of VIZIMPRO 2 mg to 60 mg orally once daily (0.04 to 1.3 times the recommended dose) across dacomitinib studies in patients with cancer. At a dose of 45 mg orally once daily, the geometric mean [coefficient of variation (CV%)] Cmax was 108 ng/mL (35%) and the AUC0–24h was 2213 ng∙h/mL (35%) at steady state in a dose-finding clinical study conducted in patients with solid tumors. Steady state was achieved within 14 days following repeated dosing and the estimated geometric mean (CV%) accumulation ratio was 5.7 (28%) based on AUC.

Absorption

The mean absolute bioavailability of dacomitinib is 80% after oral administration. The median dacomitinib time to reach maximum concentration (Tmax) occurred at approximately 6.0 hours (range 2.0 to 24 hours) after a single oral dose of VIZIMPRO 45 mg in patients with cancer.

Effect of Food

Administration of VIZIMPRO with a high-fat, high-calorie meal (approximately 800 to 1000 calories with 150, 250, and 500 to 600 calories from protein, carbohydrate and fat, respectively) had no clinically meaningful effect on dacomitinib pharmacokinetics.

Distribution

The geometric mean (CV%) volume of distribution of dacomitinib (Vss) was 1889 L (18%). In vitro binding of dacomitinib to human plasma proteins is approximately 98% and is independent of drug concentrations from 250 ng/mL to 1000 ng/mL.

Elimination

Following a single 45 mg oral dose of VIZIMPRO in patients with cancer, the mean (CV%) plasma half-life of dacomitinib was 70 hours (21%), and the geometric mean (CV%) apparent plasma clearance of dacomitinib was 24.9 L/h (36%).

Metabolism

Hepatic metabolism is the main route of clearance of dacomitinib, with oxidation and glutathione conjugation as the major pathways. Following oral administration of a single 45 mg dose of [^14C] dacomitinib, the most abundant circulating metabolite was O-desmethyl dacomitinib, which had similar in vitro pharmacologic activity as dacomitinib. The steady-state plasma trough concentration of O-desmethyl dacomitinib ranges from 7.4% to 19% of the parent. In vitro studies indicated that cytochrome P450 (CYP) 2D6 was the major isozyme involved in the formation of O-desmethyl dacomitinib, while CYP3A4 contributed to the formation of other minor oxidative metabolites.

Excretion

Following a single oral 45 mg dose of [^14C] radiolabeled dacomitinib, 79% of the radioactivity was recovered in feces (20% as dacomitinib) and 3% in urine (<1% as dacomitinib).

Specific Populations

Patients with Renal Impairment

Based on population pharmacokinetic analyses, mild (60 mL/min ≤CLcr <90 mL/min; N=590) and moderate (30 mL/min ≤CLcr <60 mL/min; N=218) renal impairment did not alter dacomitinib pharmacokinetics, relative to the pharmacokinetics in patients with normal renal function (CLcr ≥90 mL/min; N=567). The pharmacokinetics of dacomitinib has not been adequately characterized in patients with severe renal impairment (CLcr <30 mL/min) (N=4) or studied in patients requiring hemodialysis.

Patients with Hepatic Impairment

No clinically significant differences in the pharmacokinetics of dacomitinib were observed in subjects with mild, moderate or severe hepatic impairment (Child-Pugh A, B or C) [see Use in Specific Populations (8.7)].

Drug Interaction Studies

Clinical Studies

Effect of Acid-Reducing Agents on Dacomitinib

Coadministration of a single 45 mg dose of VIZIMPRO with multiple doses of rabeprazole (a proton pump inhibitor) decreased dacomitinib Cmax by 51% and AUC0–96h by 39% [see Dosage and Administration (2.4) and Drug Interactions (7.1)].

Coadministration of VIZIMPRO with a local antacid (Maalox® Maximum Strength, 400 mg/5 mL) did not cause clinically relevant changes dacomitinib concentrations [see Dosage and Administration (2.4) and Drug Interactions (7.1)].

The effect of H2 receptor antagonists on dacomitinib pharmacokinetics has not been studied [see Dosage and Administration (2.4) and Drug Interactions (7.1)].

Effect of Strong CYP2D6 Inhibitors on Dacomitinib

Coadministration of a single 45 mg dose of VIZIMPRO with multiple doses of paroxetine (a strong CYP2D6 inhibitor) in healthy subjects increased the total AUClast of dacomitinib plus its active metabolite (O-desmethyl dacomitinib) in plasma by approximately 6%, which is not considered clinically relevant.

Effect of Dacomitinib on CYP2D6 Substrates

Coadministration of a single 45 mg oral dose of VIZIMPRO increased dextromethorphan (a CYP2D6 substrate) Cmax by 9.7-fold and AUClast by 9.6-fold [see Drug Interactions (7.2)].

In Vitro Studies

Effect of Dacomitinib and O-desmethyl Dacomitinib on CYP Enzymes: Dacomitinib and its metabolite O-desmethyl dacomitinib do not inhibit CYP1A2, CYP2B6, CYP2C8, CYP2C9, CYP2C19, or CYP3A4/5. Dacomitinib does not induce CYP1A2, CYP2B6, or CYP3A4.

Effect of Dacomitinib on Uridine 5' diphospho-glucuronosyltransferase (UGT) Enzymes: Dacomitinib inhibits UGT1A1. Dacomitinib does not inhibit UGT1A4, UGT1A6, UGT1A9, UGT2B7, or UGT2B15.

Effect of Dacomitinib on Transporter Systems: Dacomitinib is a substrate for the membrane transport protein P-glycoprotein (P-gp) and Breast Cancer Resistance Protein (BCRP). Dacomitinib inhibits P-gp, BCRP, and organic cation transporter (OCT)1. Dacomitinib does not inhibit organic anion transporters (OAT)1 and OAT3, OCT2, organic anion transporting polypeptide (OATP)1B1, and OATP1B3.

13 NONCLINICAL TOXICOLOGY

13.1 Carcinogenesis, Mutagenesis, Impairment of Fertility

Carcinogenicity studies have not been performed with VIZIMPRO.

Dacomitinib was not mutagenic in a bacterial reverse mutation (Ames) assay or clastogenic in an in vitro human lymphocyte chromosome aberration assay or clastogenic or aneugenic in an in vivo rat bone marrow micronucleus assay.

Daily oral administration of dacomitinib at doses ≥0.5 mg/kg/day to female rats (approximately 0.14 times the exposure based on AUC at the 45 mg human dose) resulted in reversible epithelial atrophy in the cervix and vagina. Oral administration of dacomitinib at 2 mg/kg/day to male rats (approximately 0.6 times the human exposure based on AUC at the 45 mg clinical dose) resulted in reversible decreased secretion in the prostate gland.

14 CLINICAL STUDIES

The efficacy of VIZIMPRO was demonstrated in a randomized, multicenter, multinational, open-label study (ARCHER 1050; [NCT01774721]). Patients were required to have unresectable, metastatic NSCLC with no prior therapy for metastatic disease or recurrent disease with a minimum of 12 months disease-free after completion of systemic therapy; an Eastern Cooperative Oncology Group (ECOG) performance status of 0 or 1; EGFR exon 19 deletion or exon 21 L858R substitution mutations. EGFR mutation status was prospectively determined by local laboratory or commercially available tests (e.g., therascreen® EGFR RGQ PCR and cobas® EGFR Mutation Test).

Patients were randomized (1:1) to receive VIZIMPRO 45 mg orally once daily or gefitinib 250 mg orally once daily until disease progression or unacceptable toxicity. Randomization was stratified by region (Japanese versus mainland Chinese versus other East Asian versus non-East Asian), and EGFR mutation status (exon 19 deletions versus exon 21 L858R substitution mutation). The major efficacy outcome measure was progression-free survival (PFS) as determined by blinded Independent Radiologic Central (IRC) review per RECIST v1.1. Additional efficacy outcome measures were overall response rate (ORR), duration of response (DoR), and overall survival (OS).

A total of 452 patients were randomized to receive VIZIMPRO (N=227) or gefitinib (N=225). The demographic characteristics were 60% female; median age 62 years (range: 28 to 87), with 40% aged 65 years and older; and 23% White, 77% Asian, and less than 1% Black. Prognostic and tumor characteristics were ECOG performance status 0 (30%) or 1 (70%); 59% with exon 19 deletion and 41% with exon 21 L858R substitution; Stage IIIB (8%) and Stage IV (92%); 64% were never smokers; and 1% received prior adjuvant or neoadjuvant therapy.

ARCHER 1050 demonstrated a statistically significant improvement in PFS as determined by the IRC. Results are summarized in Table 5 and Figures 1 and 2.

The hierarchical statistical testing order was PFS followed by ORR and then OS. No formal testing of OS was conducted since the formal comparison of ORR was not statistically significant.

Table 5. Efficacy Results in ARCHER 1050
 | VIZIMPRO N=227 | Gefitinib N=225
Progression-Free Survival (per IRC)
Number of patients with event, n (%) | 136 (59.9%) | 179 (79.6%)
Median PFS in months (95% CI) | 14.7 (11.1, 16.6) | 9.2 (9.1, 11.0)
HR (95% CI) [From stratified Cox Regression.] | 0.59 (0.47, 0.74)
p-value [Based on the stratified log-rank test.] | <0.0001
Overall Response Rate (per IRC)
Overall Response Rate % (95% CI) | 75% (69, 80) | 72% (65, 77)
p-value [Based on the stratified Cochran-Mantel-Haenszel test.] | 0.39
Duration of Response in Responders (per IRC)
Median DoR in months (95% CI) | 14.8 (12.0, 17.4) | 8.3 (7.4, 9.2)
CI=confidence interval; DoR=duration of response; HR=hazard ratio; IRC=Independent Radiologic Central; N/n=total number; PFS=progression-free survival.

Figure 1. Kaplan-Meier Curve for PFS per IRC Review in ARCHER 1050

Figure 2. Kaplan-Meier Curve for OS in ARCHER 1050

16 HOW SUPPLIED/STORAGE AND HANDLING

VIZIMPRO is supplied in strengths and package configurations as described in Table 6 below:

Table 6. VIZIMPRO Strengths and Package Configurations
VIZIMPRO Tablets
Package Configuration | Tablet Strength (mg) | NDC | Tablet Description
30-Count Bottle with a child-resistant closure | 15 | 0069-0197-30 | Blue film-coated, immediate release, round biconvex tablet, debossed with "Pfizer" on one side and "DCB15" on the other side.
30-Count Bottle with a child-resistant closure | 30 | 0069-1198-30 | Blue film-coated immediate release, round biconvex tablet, debossed with "Pfizer" on one side and "DCB30" on the other side.
30-Count Bottle with a child-resistant closure | 45 | 0069-2299-30 | Blue film-coated immediate release, round biconvex tablet, debossed with "Pfizer" on one side and "DCB45" on the other side.

STORAGE AND HANDLING

Store at 20 °C to 25 °C (68 °F to 77 °F); excursions permitted between 15 °C to 30 °C (59 °F to 86 °F). [see USP Controlled Room Temperature].

17 PATIENT COUNSELING INFORMATION

Advise the patient to read the FDA-approved patient labeling (Patient Information).

Interstitial Lung Disease (ILD)

- Advise patients of the risks of severe or fatal ILD, including pneumonitis. Advise patients to contact their healthcare provider immediately to report new or worsening respiratory symptoms [see Warnings and Precautions (5.1)].

Diarrhea

- Advise patients to contact their healthcare provider at the first signs of diarrhea. Advise patients that intravenous hydration and/or anti-diarrheal medication (e.g., loperamide) may be required to manage diarrhea [see Warnings and Precautions (5.2)].

Dermatologic Adverse Reactions

- Advise patients to initiate use of moisturizers and to minimize sun exposure with protective clothing and use of sunscreen at the time of initiation of VIZIMPRO. Advise patients to contact their healthcare provider immediately to report new or worsening rash, erythematous and exfoliative reactions [see Warning and Precautions (5.3)].

Drug Interactions

- Advise patients to avoid use of PPIs while taking VIZIMPRO. Short-acting antacids or H2 receptor antagonists may be used if needed. Advise patients to take VIZIMPRO at least 6 hours before or 10 hours after taking an H2-receptor antagonist [see Drug Interactions (7.1)].

Embryo-Fetal Toxicity

- Advise females of reproductive potential that VIZIMPRO can result in fetal harm and to use effective contraception during treatment with VIZIMPRO and for 17 days after the last dose of VIZIMPRO. Advise females of reproductive potential to contact their healthcare provider with a known or suspected pregnancy [see Use in Specific Populations (8.1 and 8.3)].

Lactation

- Advise women not to breastfeed during treatment with VIZIMPRO and for 17 days after the last dose of VIZIMPRO [see Use in Specific Populations (8.2)].

This product's labeling may have been updated. For the most recent prescribing information, please visit www.VIZIMPRO.com.

LAB-1237-2.0

PATIENT INFORMATION
VIZIMPRO® (vih-ZIM-pro)
(dacomitinib)
tablets

What is VIZIMPRO?
VIZIMPRO is a prescription medicine used to treat non-small cell lung cancer (NSCLC) that has spread to other parts of the body (metastatic):

- As your first treatment if your tumor has certain types of abnormal epidermal growth factor receptor (EGFR) gene(s).

Your healthcare provider will perform a test to make sure that VIZIMPRO is right for you.
It is not known if VIZIMPRO is safe and effective in children.

Before taking VIZIMPRO, tell your healthcare provider about all your medical conditions, including if you:

- have frequent diarrhea.
- have a history of lung or breathing problems other than lung cancer.
- are pregnant, or plan to become pregnant. VIZIMPRO can harm your unborn baby.

Females who are able to become pregnant:

  - Your healthcare provider should do a pregnancy test before you start treatment with VIZIMPRO.
  - You should use effective birth control (contraception) during treatment and for at least 17 days after your last dose of VIZIMPRO. Talk to your healthcare provider about birth control methods that may be right for you during this time.
  - Tell your healthcare provider right away if you become pregnant during your treatment with VIZIMPRO.
- are breastfeeding or plan to breastfeed. It is not known if VIZIMPRO passes into your breast milk. Do not breastfeed during treatment and for at least 17 days after your last dose of VIZIMPRO. Talk to your healthcare provider about the best way to feed your baby during this time.

Tell your healthcare provider about all of the medicines you take, including prescription and over-the-counter medicines, vitamins, and herbal supplements. VIZIMPRO and other medicines or supplements may affect each other causing side effects.

How should I take VIZIMPRO?

- Take VIZIMPRO exactly as your healthcare provider tells you.
- Take your dose at approximately the same time each day.
- Your healthcare provider may change your dose, temporarily stop, or permanently stop treatment with VIZIMPRO if you have side effects.
- Take VIZIMPRO 1 time each day with or without food.
- If you take an antacid or H2 blocker medicine during treatment with VIZIMPRO, take your dose of VIZIMPRO at least 6 hours before or 10 hours after taking the antacid or H2 blocker medicine. Do not change your dose or stop taking VIZIMPRO unless your healthcare provider tells you.
- If you vomit or miss a dose of VIZIMPRO, do not take another dose or make up for the missed dose. Take your next dose at your regular time.

What should I avoid during treatment with VIZIMPRO?

- Minimize exposure to sunlight. VIZIMPRO can cause skin reactions. See “What are the possible side effects of VIZIMPRO?”

What are the possible side effects of VIZIMPRO?
VIZIMPRO may cause serious side effects, including:

- Lung or breathing problems. VIZIMPRO may cause severe inflammation of the lung that may lead to death. Symptoms may be similar to those symptoms from lung cancer. Tell your healthcare provider right away if you have any new or worsening lung symptoms, including trouble breathing or shortness of breath, cough, or fever.
- Diarrhea. Diarrhea is common during treatment with VIZIMPRO, and can be severe and lead to death. Diarrhea can cause you to lose too much body fluid (dehydration). Your healthcare provider may tell you to start drinking more fluids or start taking your anti-diarrheal medicines. Tell your healthcare provider right away, if you have any loose stools or have stools more often than is normal for you.
- Skin reactions. Skin reactions are common with VIZIMPRO and can be severe. These skin reactions may include: dry skin, redness, rash, acne, itching, and peeling or blistering of your skin. Use moisturizers every day when taking VIZIMPRO. Use sunscreen and wear protective clothing that covers your skin, while exposed to sunlight, while you are taking VIZIMPRO. Your healthcare provider may prescribe other medicines to help skin reactions. Tell your healthcare provider right away about any worsening skin reactions.

The most common side effects of VIZIMPRO include:

- rash
- diarrhea
- mouth pain and sores
- nail inflammation
- common cold

- dry skin
- decreased appetite
- decreased weight
- dry, red, itchy eyes
- hair loss
- itching

Call your doctor for medical advice about side effects. You may report side effects to FDA at 1-800-FDA-1088.

How should I store VIZIMPRO?

- Store VIZIMPRO at 20 °C to 25 °C (68 °F to 77 °F).

Keep VIZIMPRO and all medicines out of the reach of children.

General information about the safe and effective use of VIZIMPRO.
Medicines are sometimes prescribed for purposes other than those listed in a Patient Information leaflet. Do not use VIZIMPRO for a condition for which it was not prescribed. Do not give VIZIMPRO to other people, even if they have the same symptoms you have. It may harm them.
You can ask your pharmacist or healthcare provider for more information about VIZIMPRO that is written for health professionals.

What are the ingredients in VIZIMPRO?
Active ingredient: dacomitinib
Inactive ingredients: lactose monohydrate, microcrystalline cellulose, sodium starch glycolate, and magnesium stearate.
Film coating contains: Opadry II® Blue 85F30716 containing: Polyvinyl alcohol – partially hydrolyzed, Talc, Titanium dioxide, Macrogol/PEG 3350, and FD&C Blue #2/Indigo Carmine Aluminum Lake.

LAB-1238-1.0
For more information, go to www.VIZIMPRO.com or call 1-800-438-1985.

This Patient Information has been approved by the U.S. Food and Drug Administration.

Issued: September 2018

PRINCIPAL DISPLAY PANEL - 15 mg Tablet Bottle Label

Pfizer
NDC 0069-0197-30

Vizimpro®
(dacomitinib) tablets

15 mg

30 Tablets
Rx only

PRINCIPAL DISPLAY PANEL - 30 mg Tablet Bottle Label

Pfizer
NDC 0069-1198-30

Vizimpro®
(dacomitinib) tablets

30 mg

30 Tablets
Rx only

PRINCIPAL DISPLAY PANEL - 45 mg Tablet Bottle Label

Pfizer
NDC 0069-2299-30

Vizimpro®
(dacomitinib) tablets

45 mg

30 Tablets
Rx only